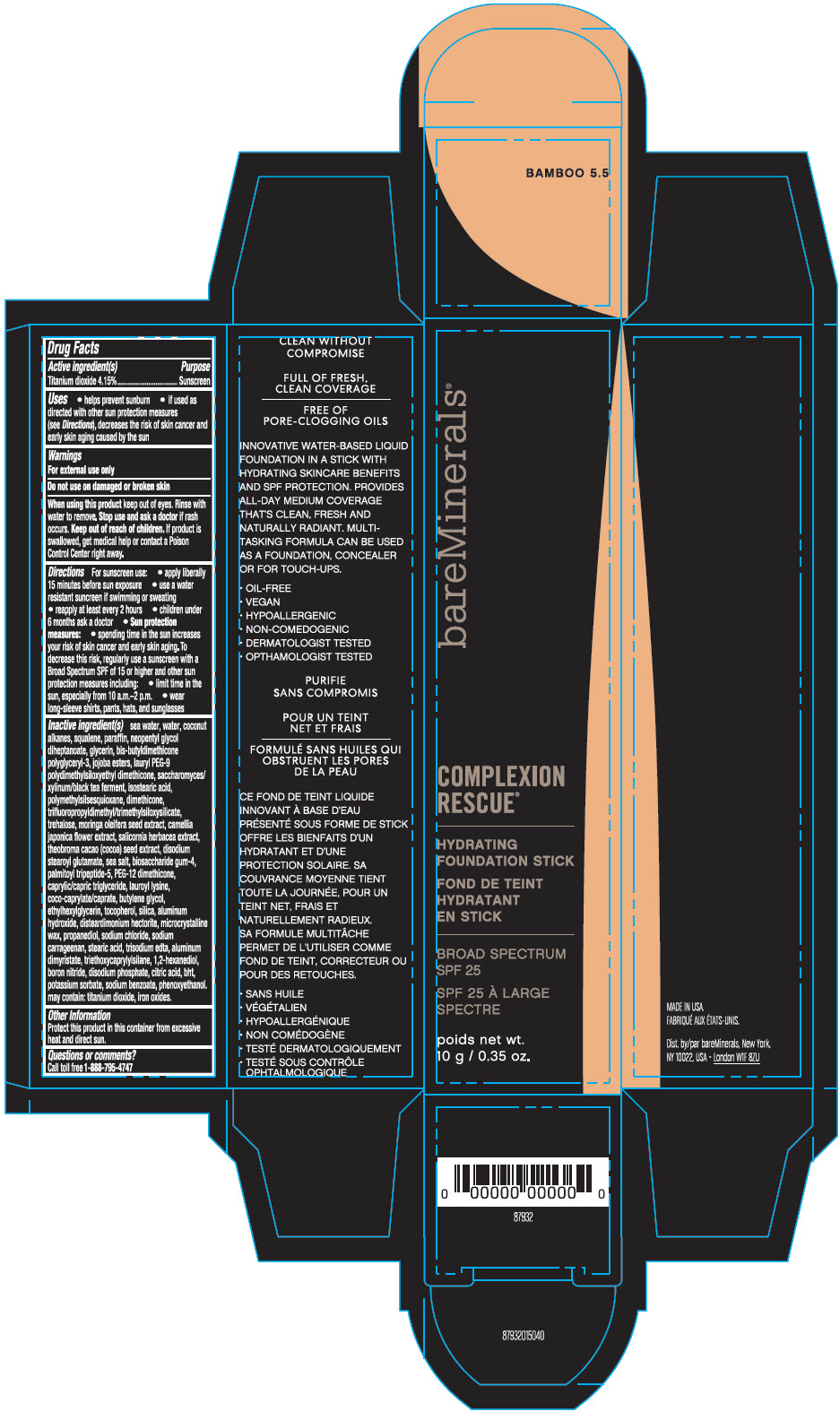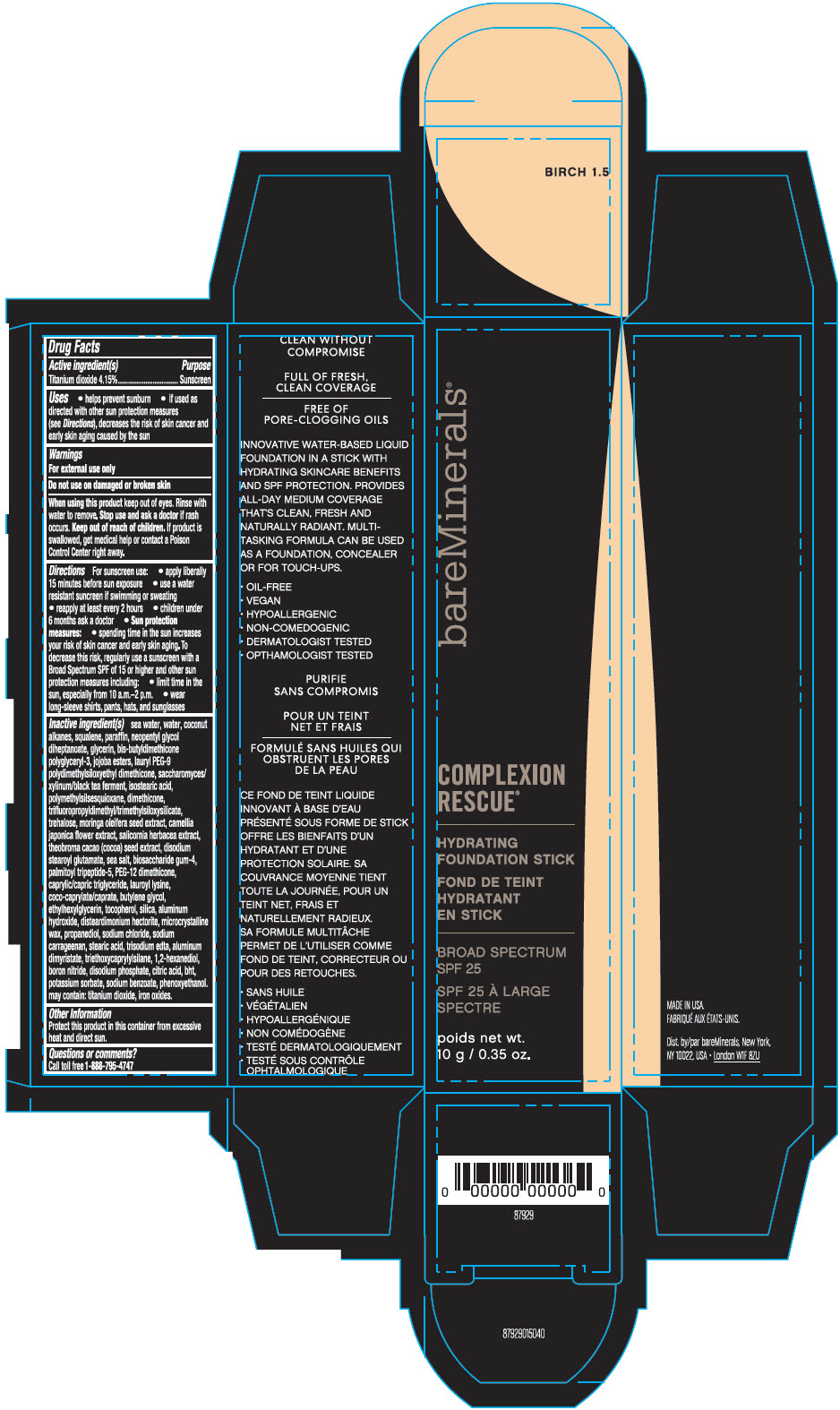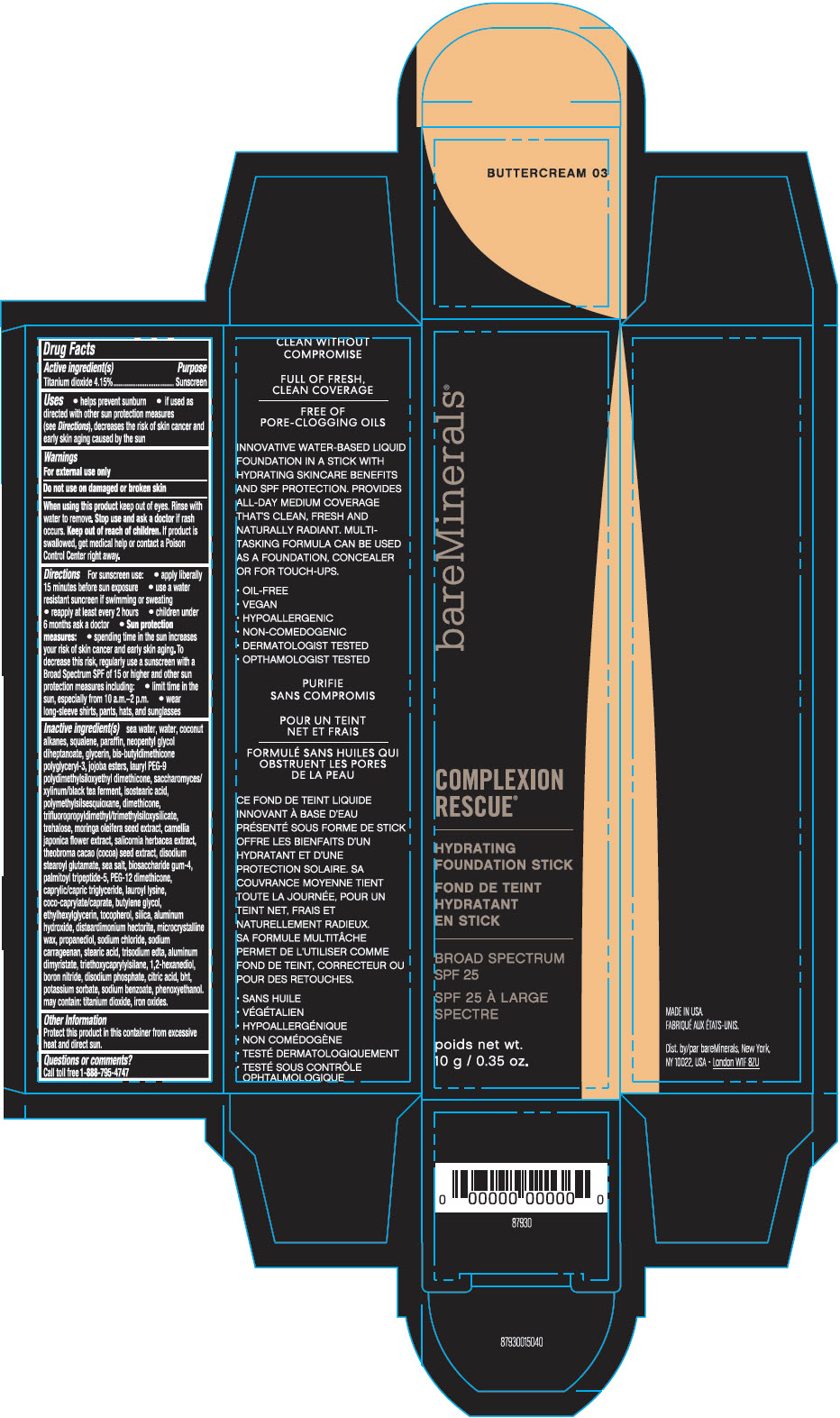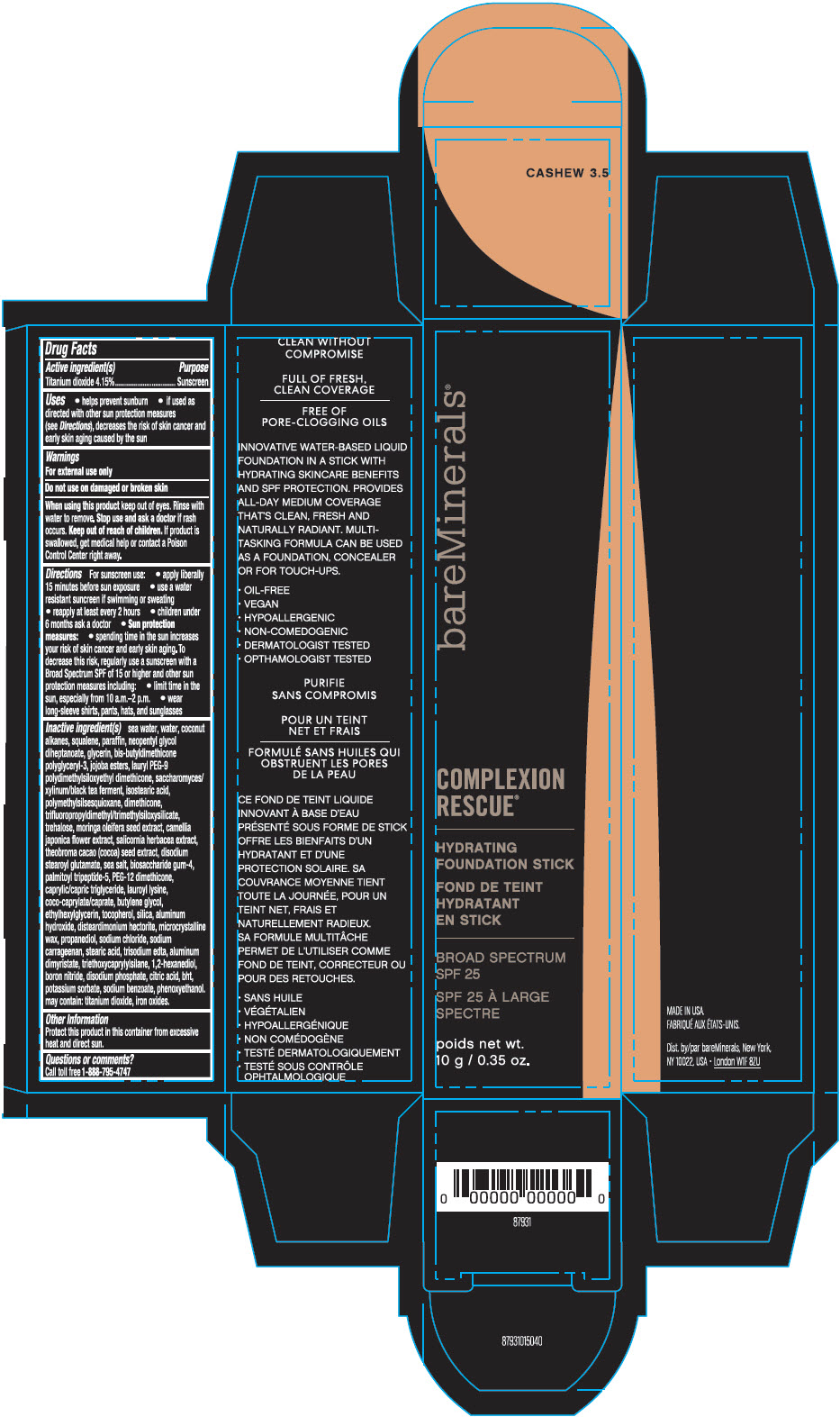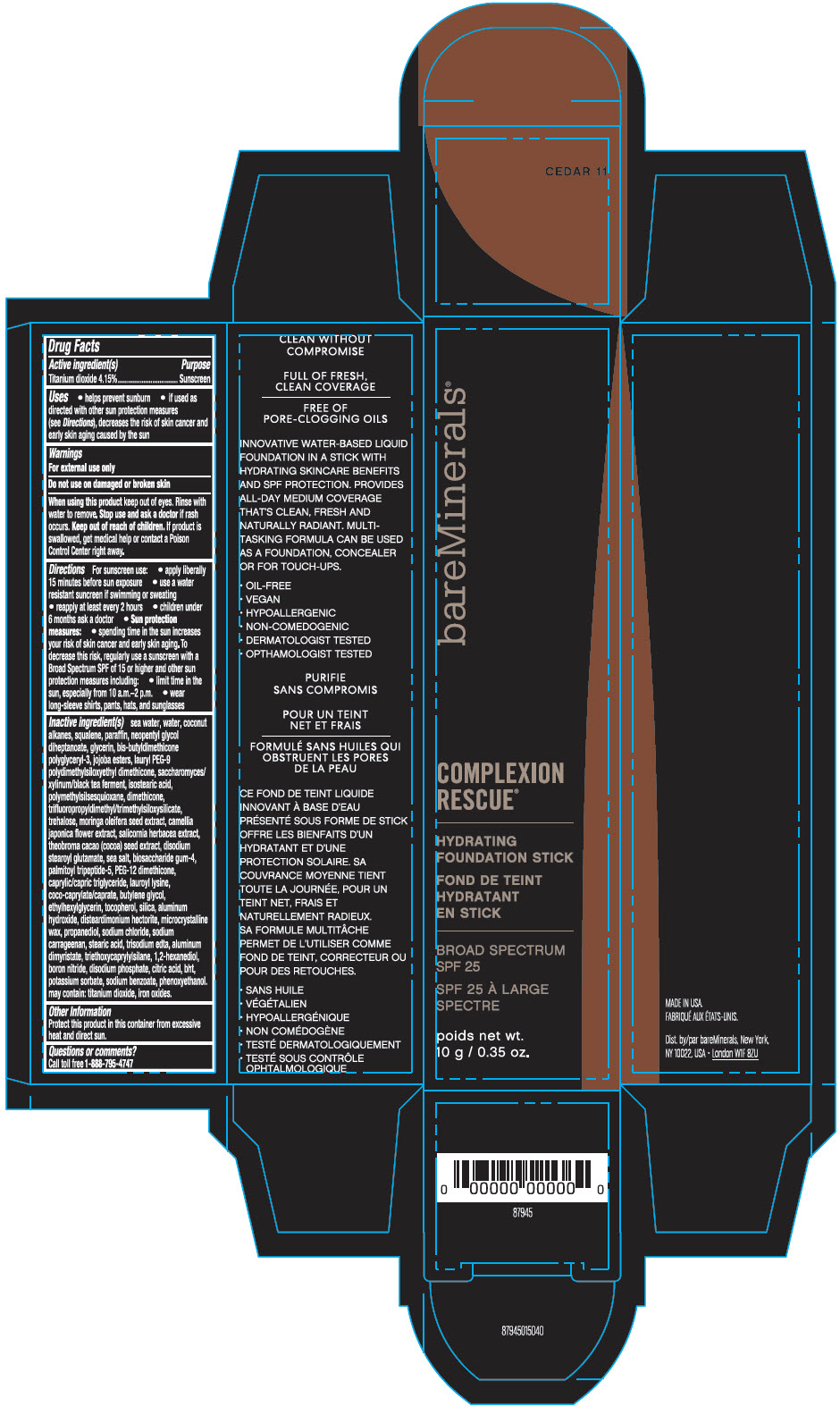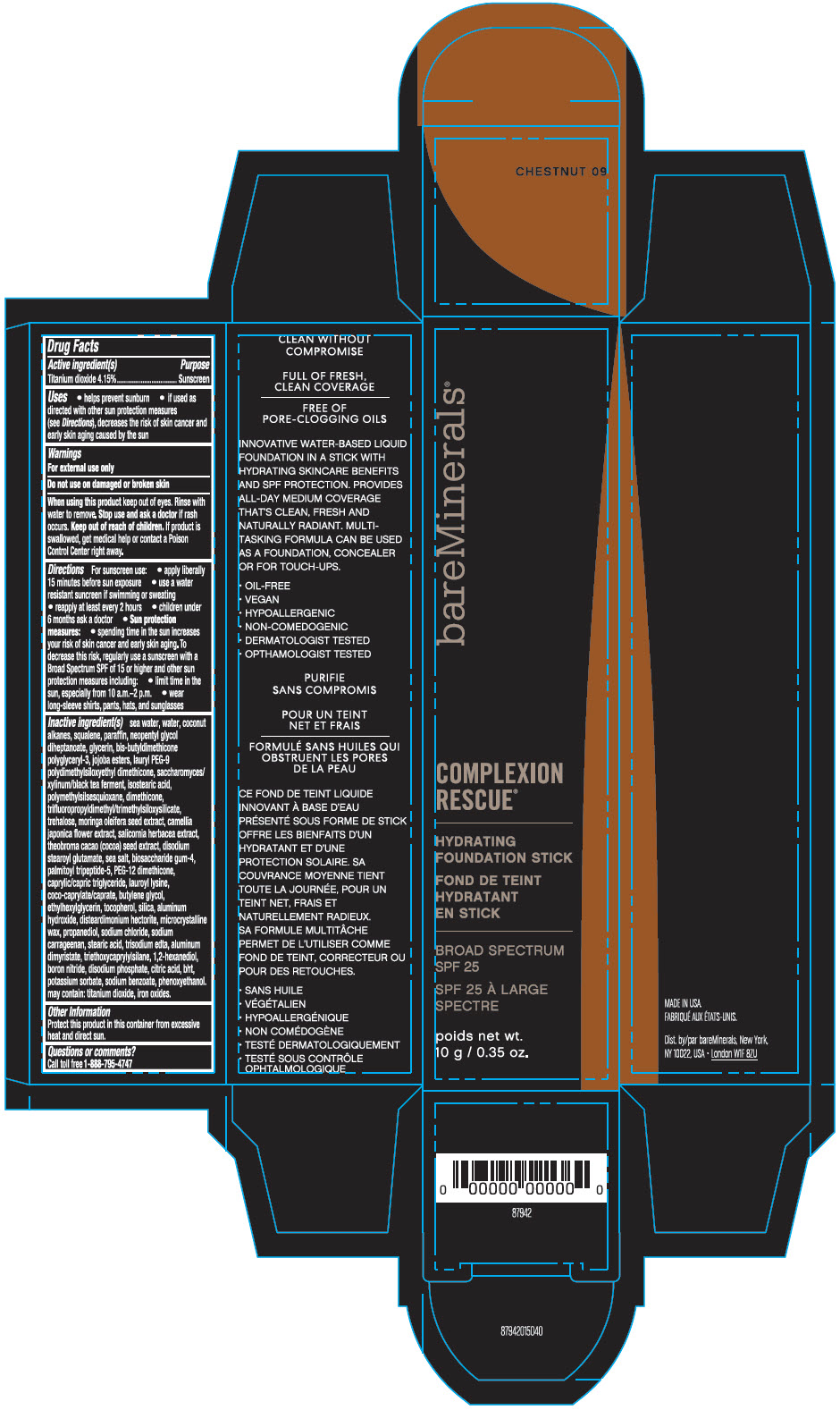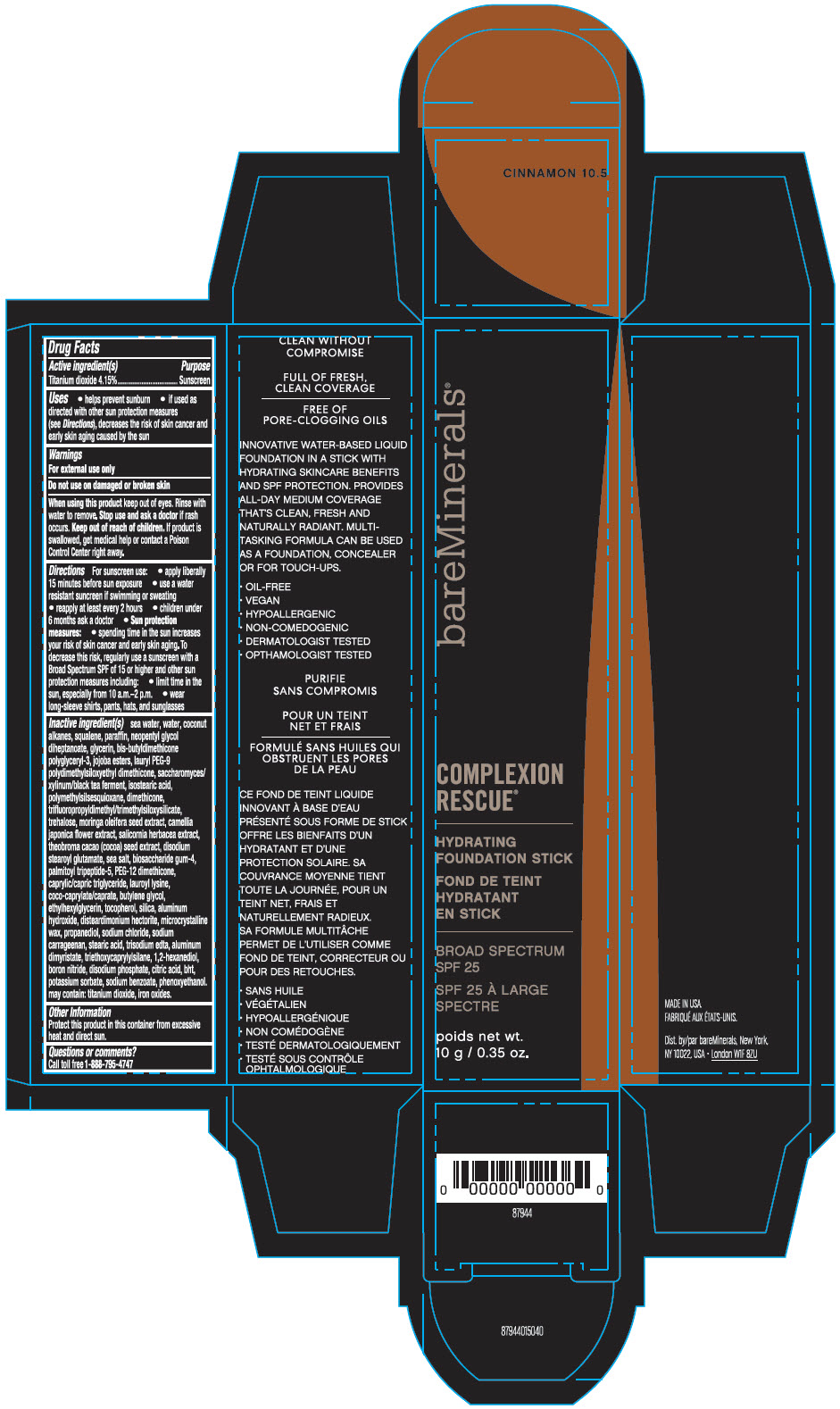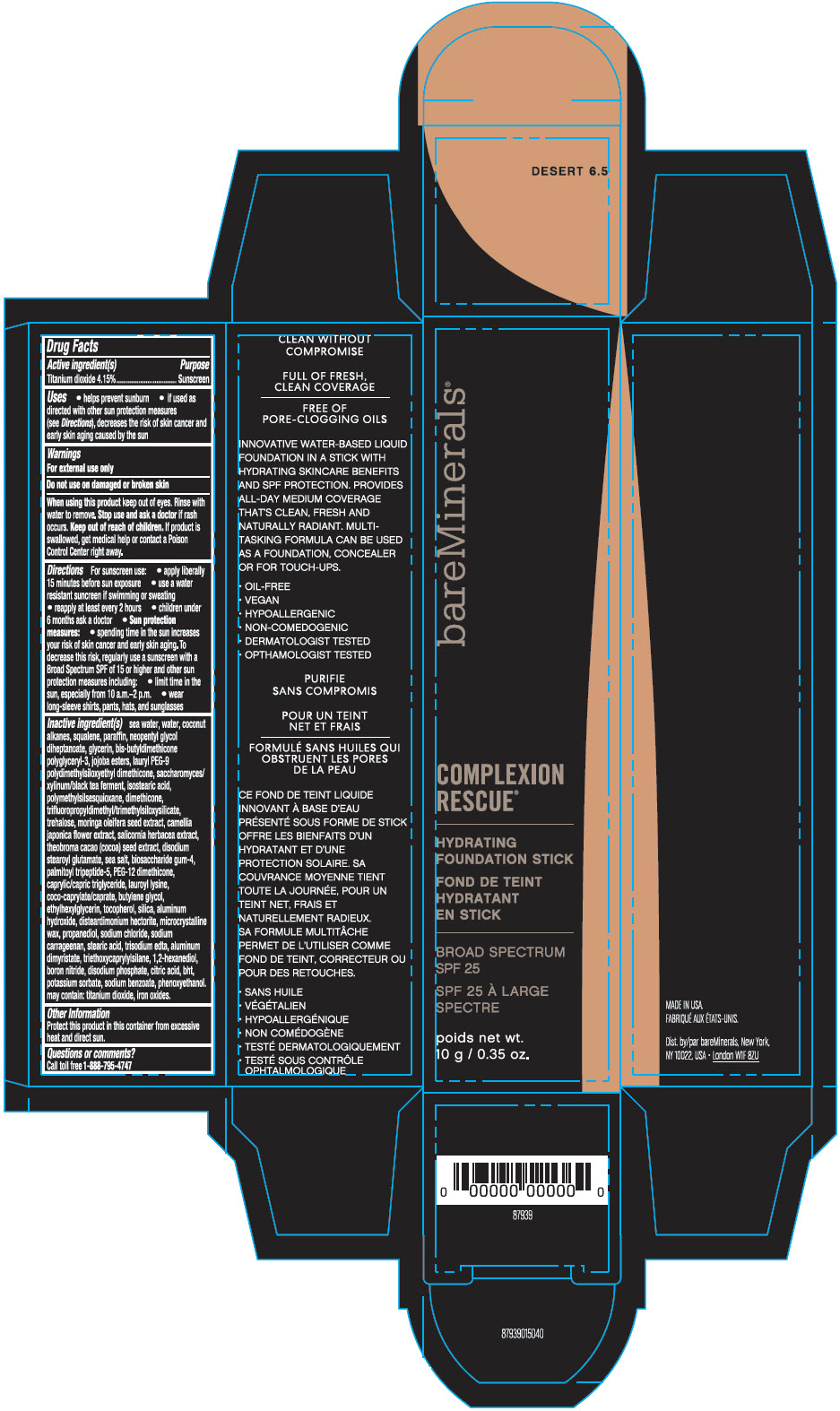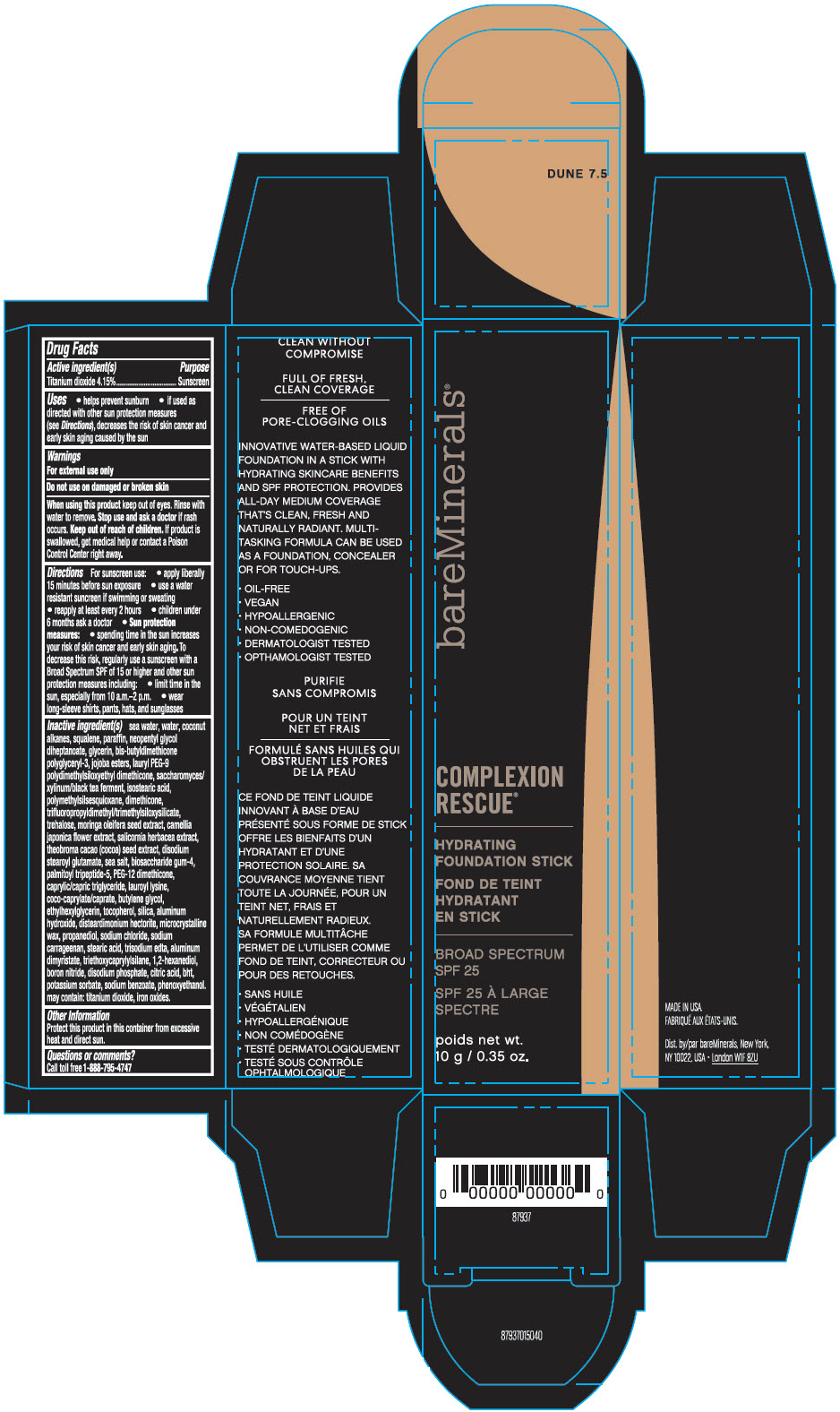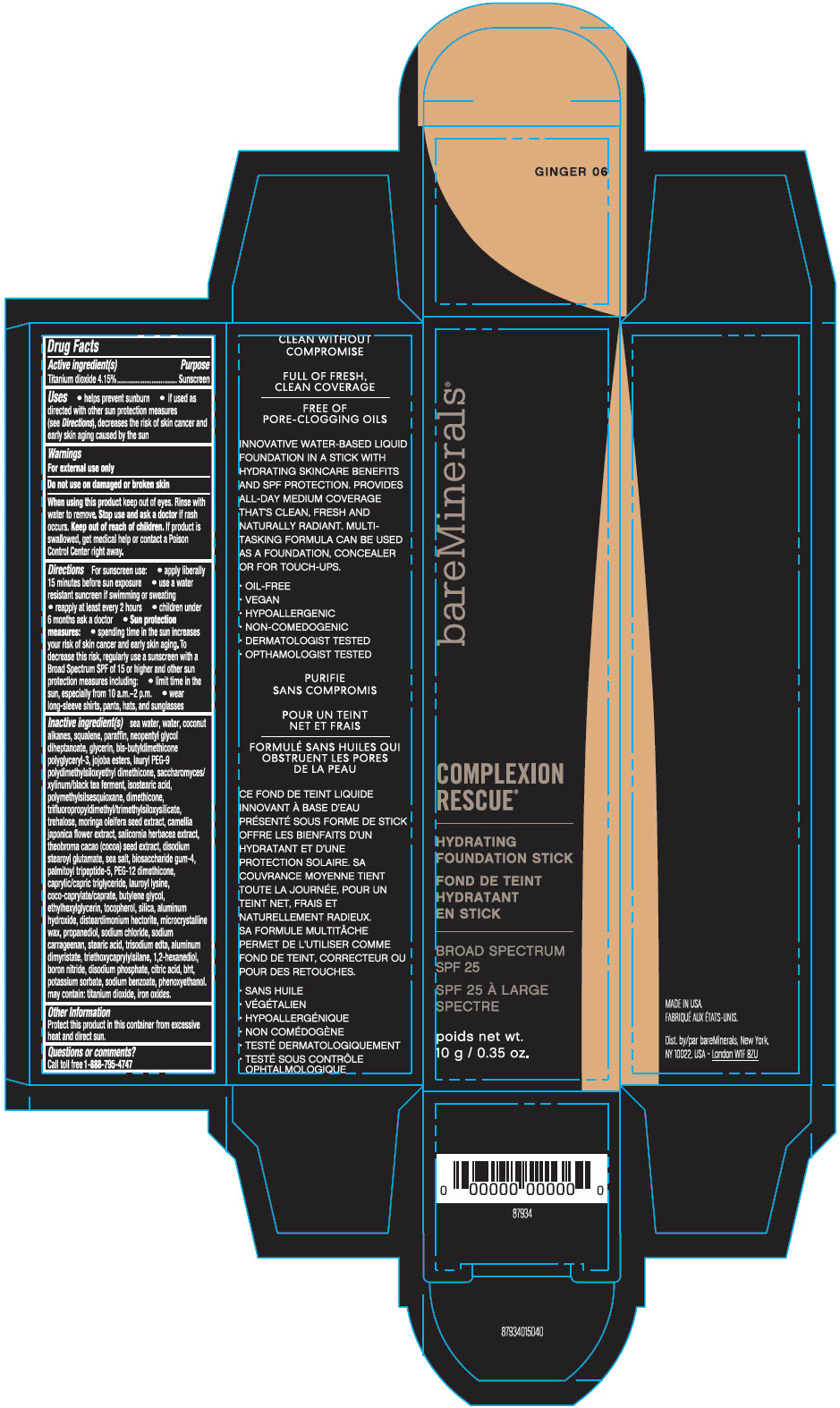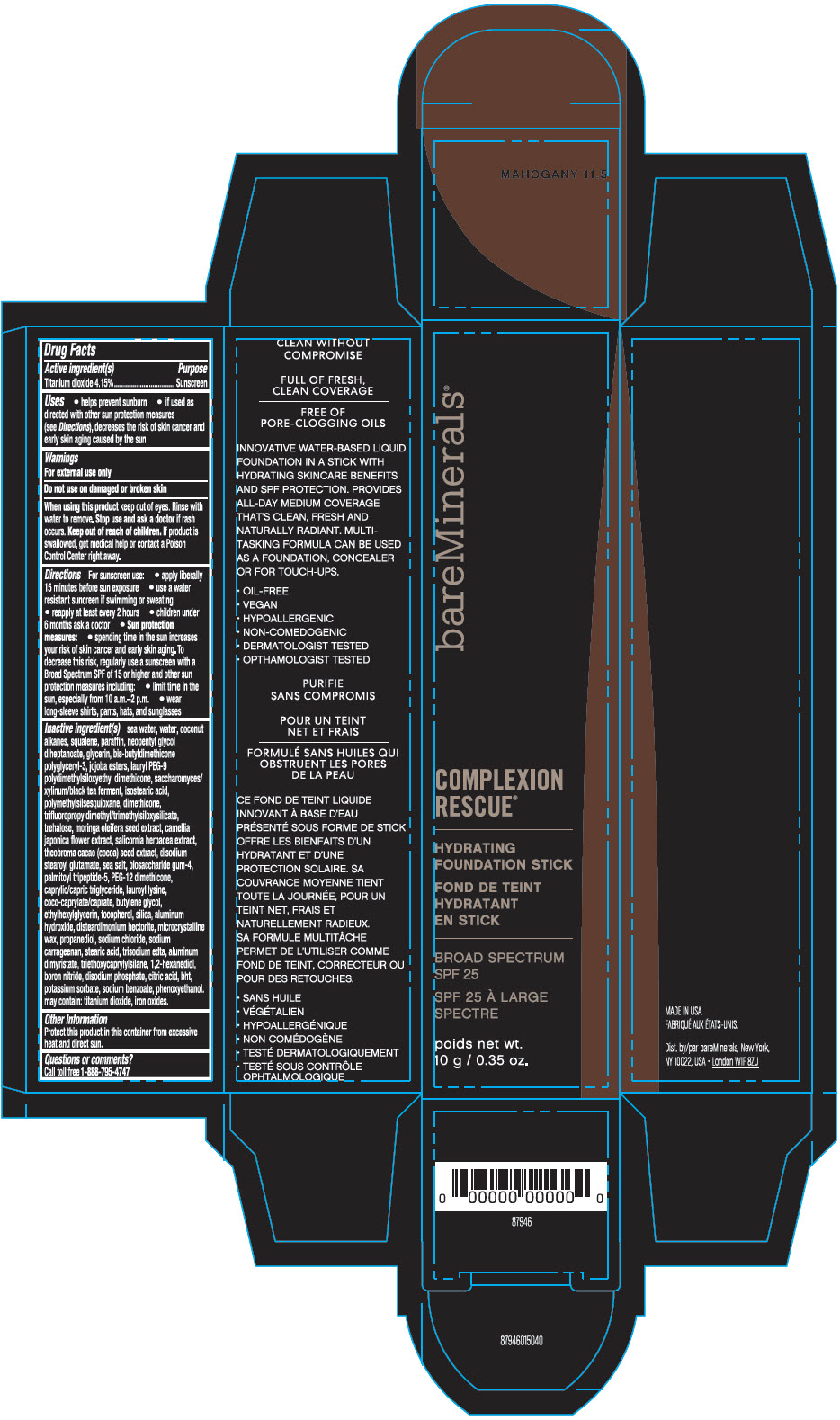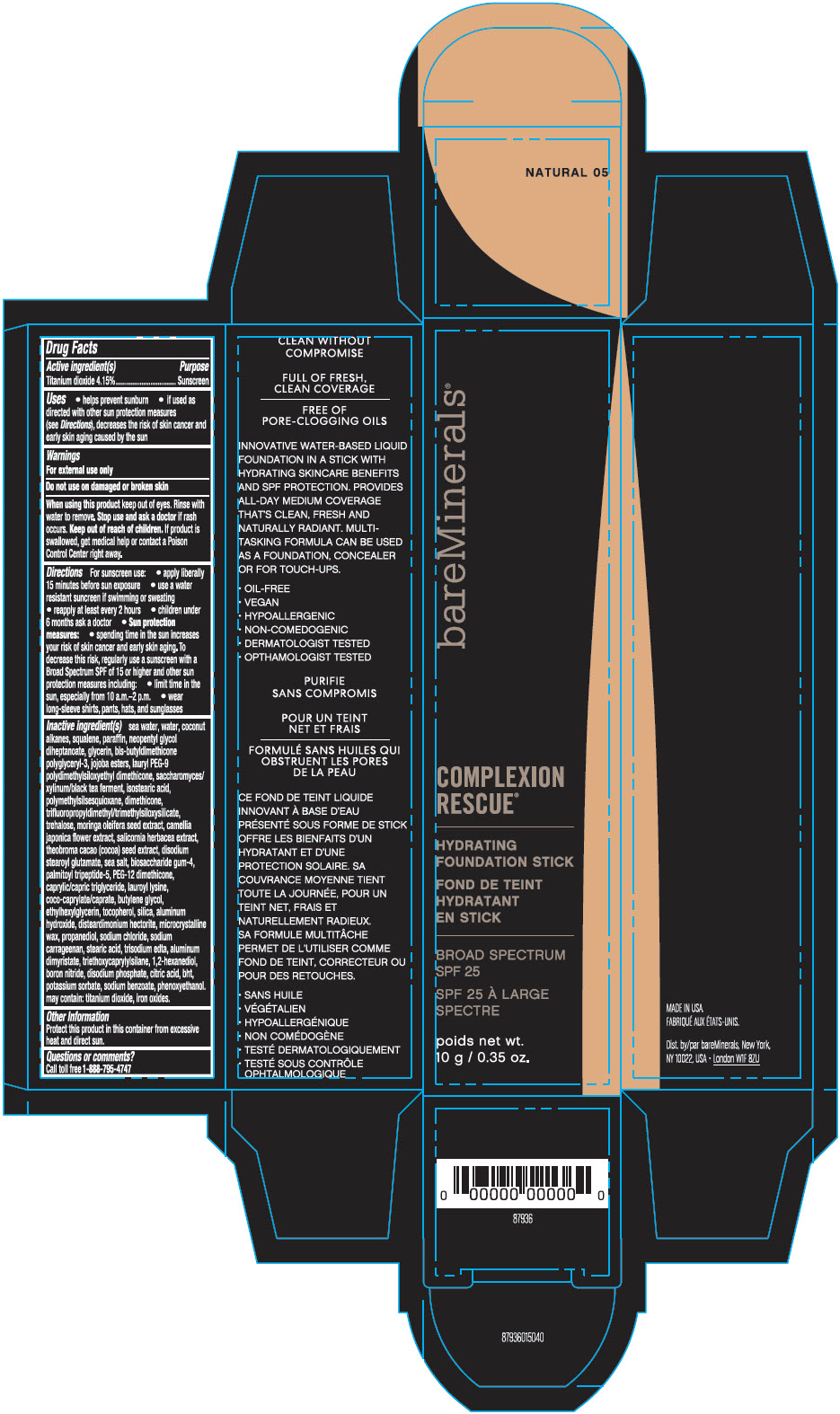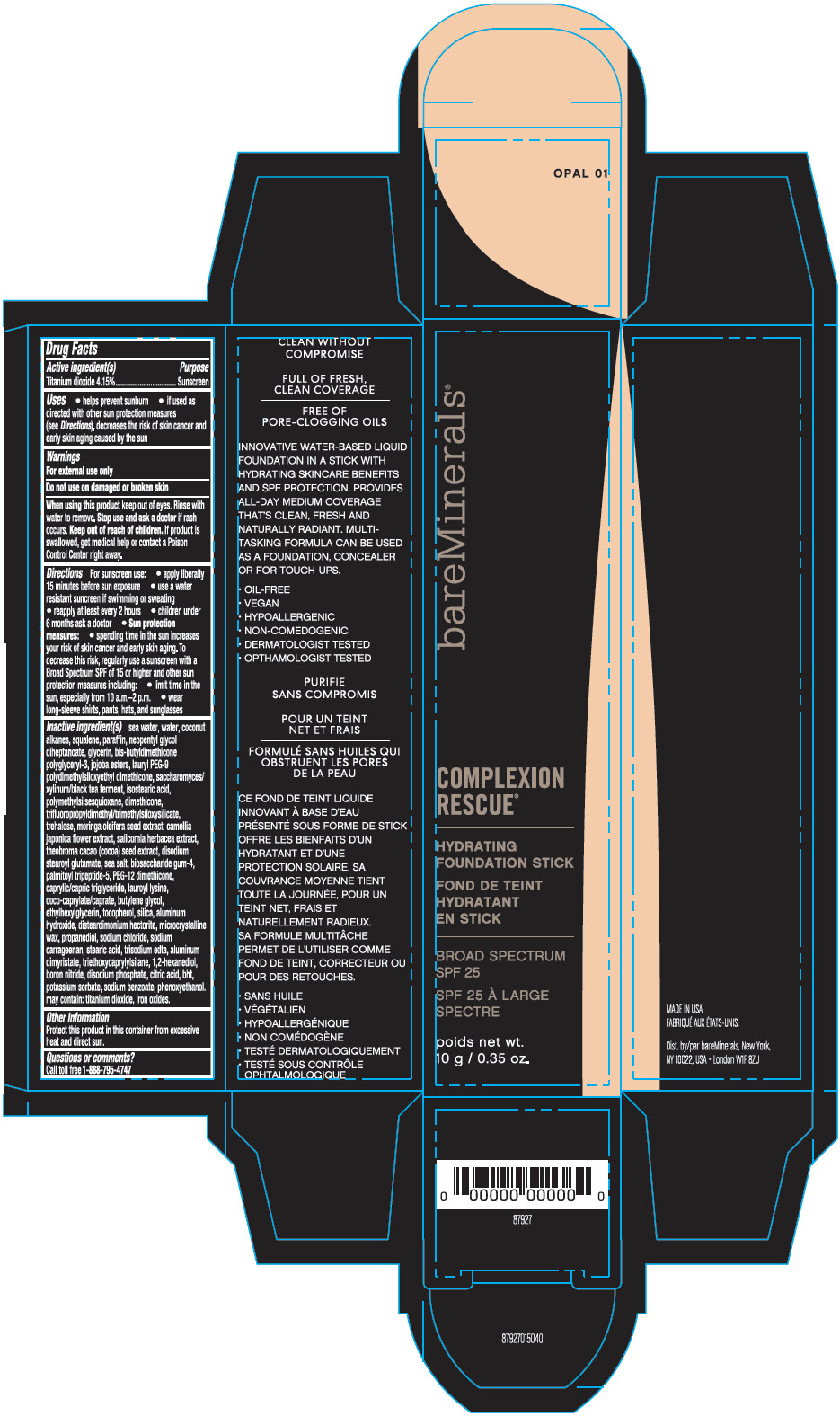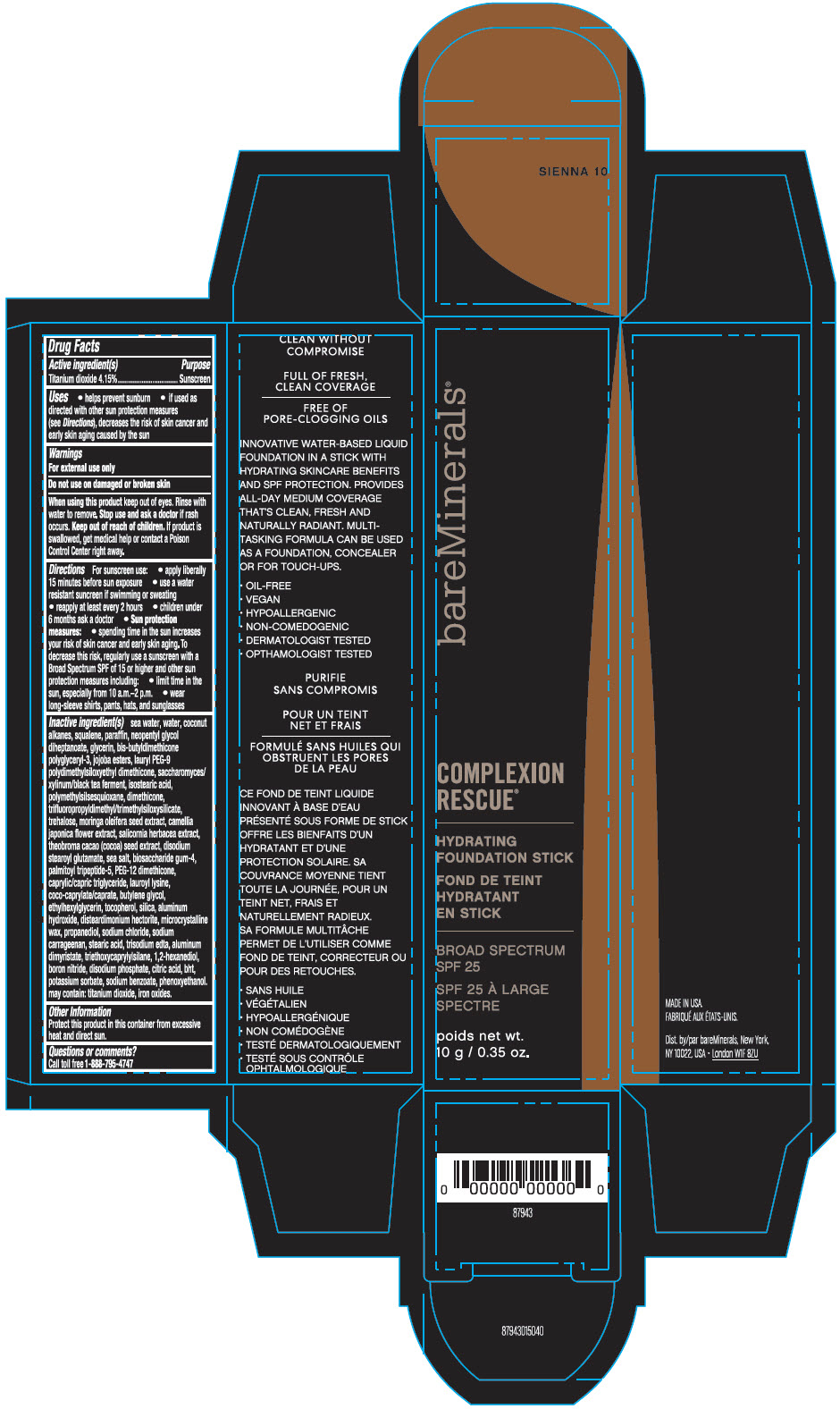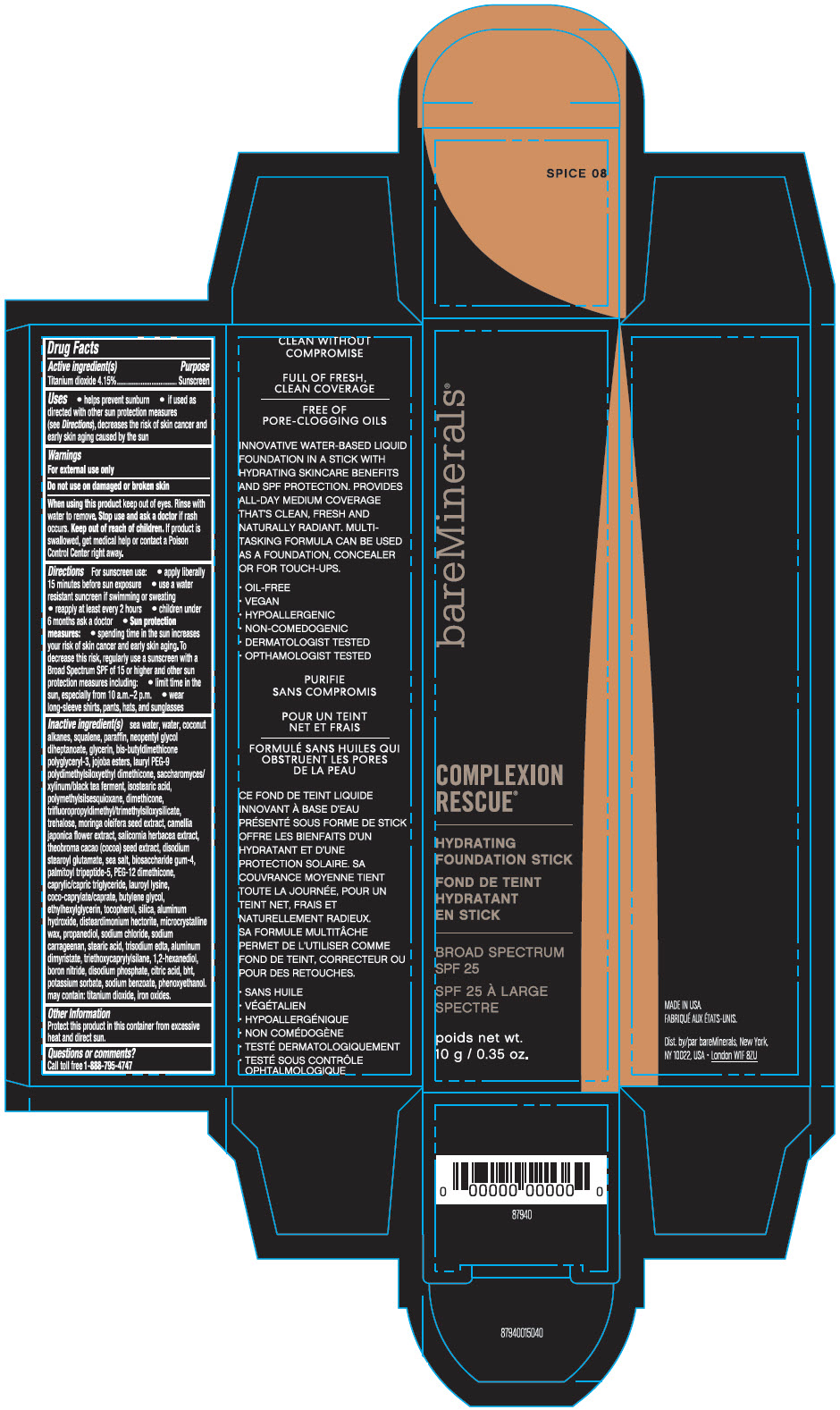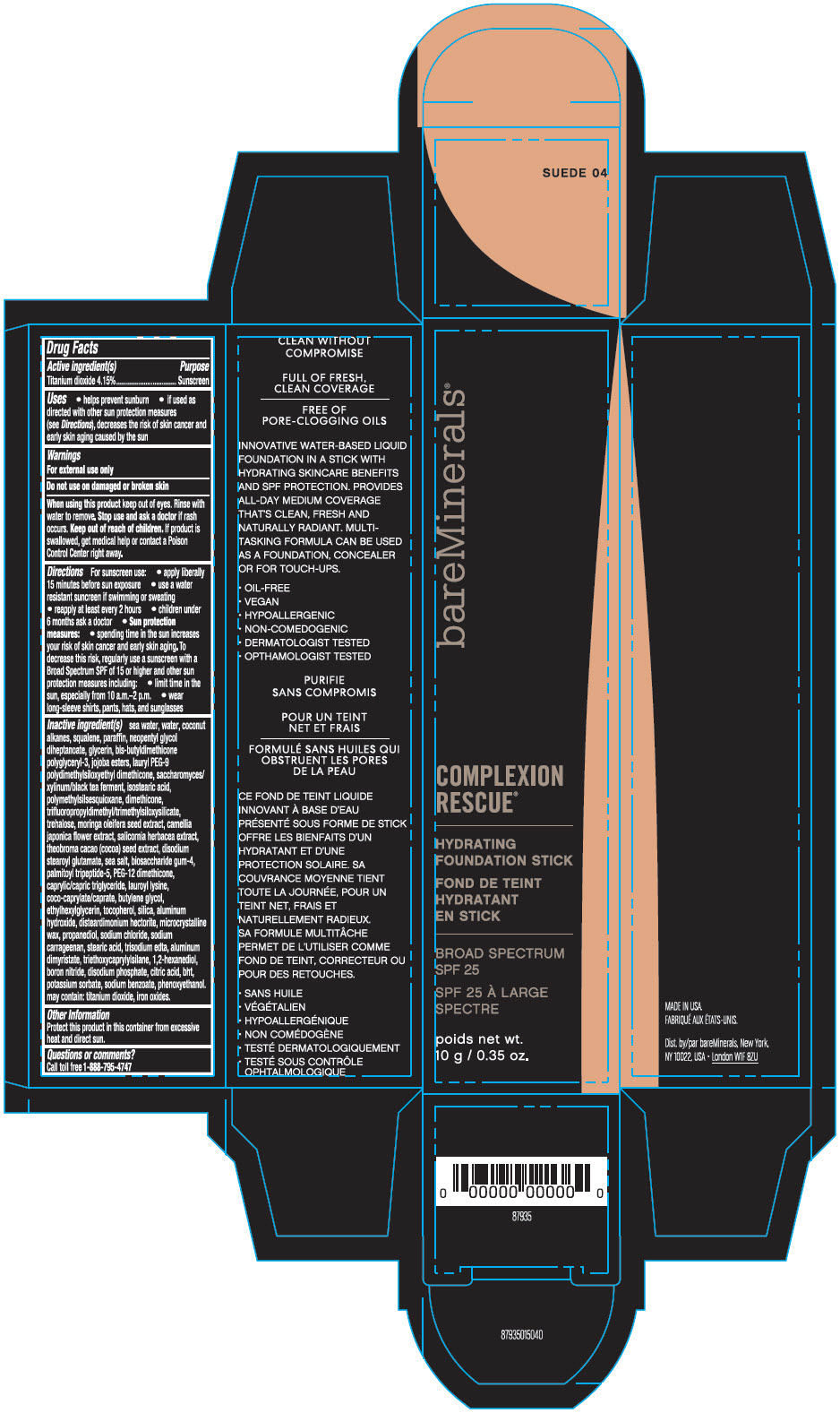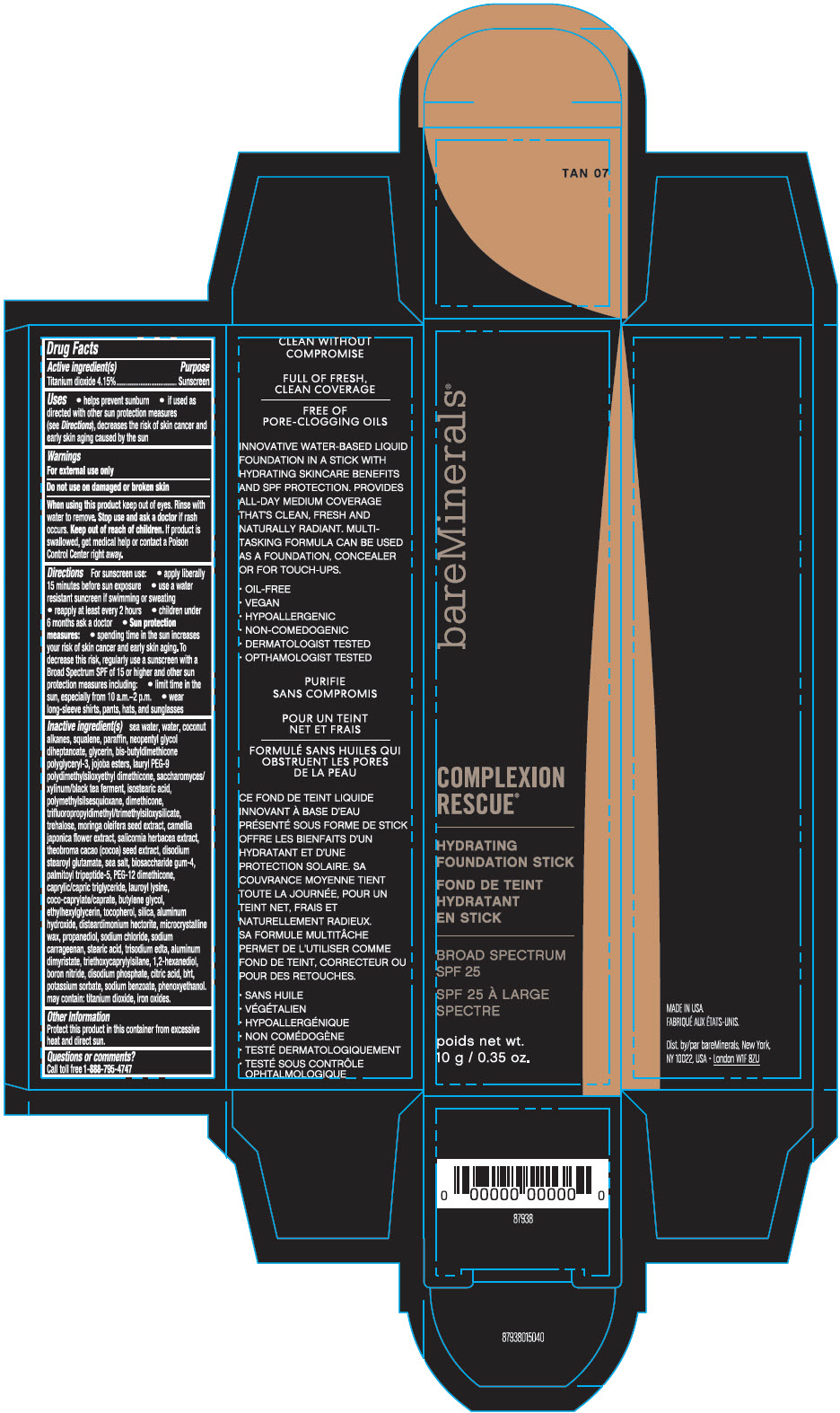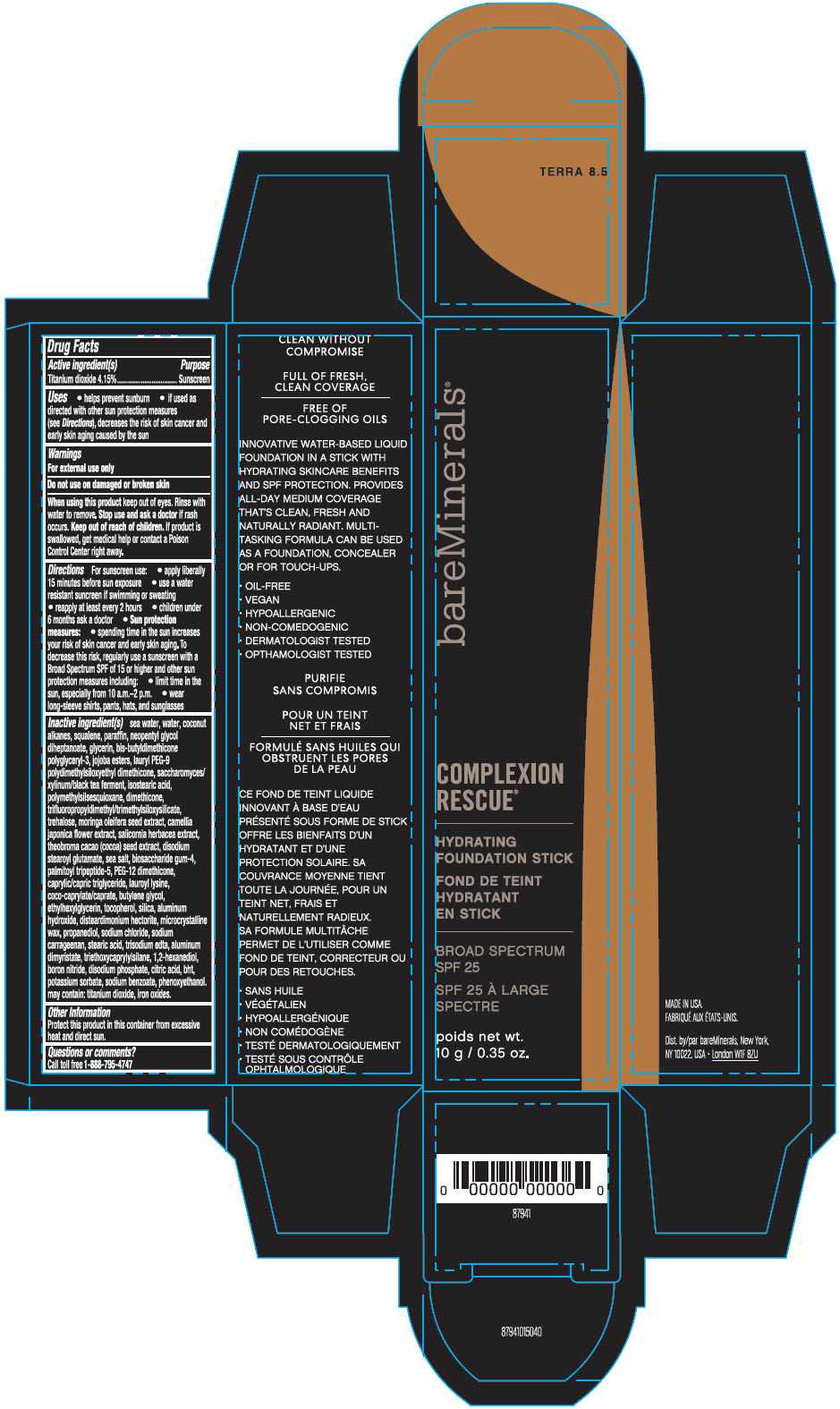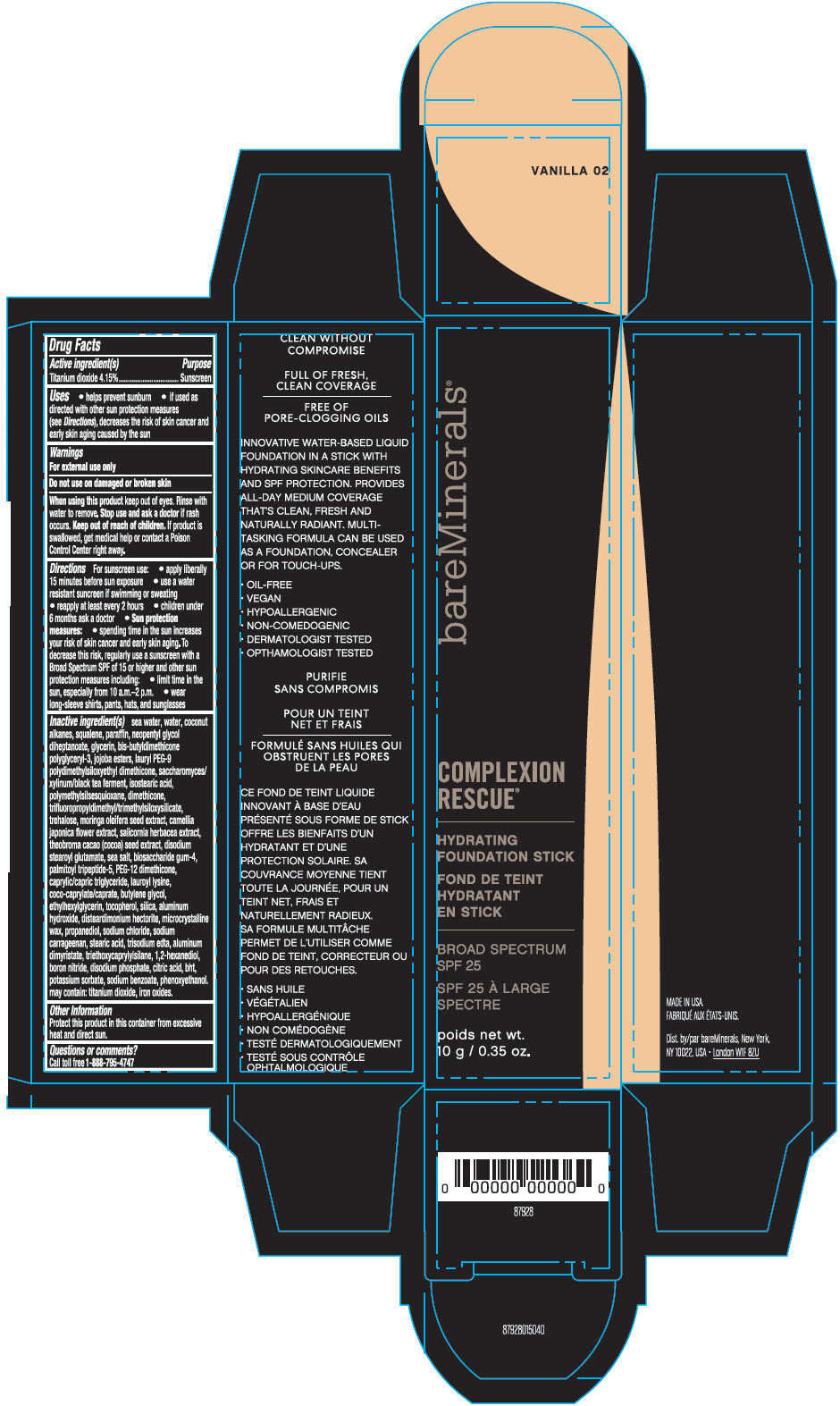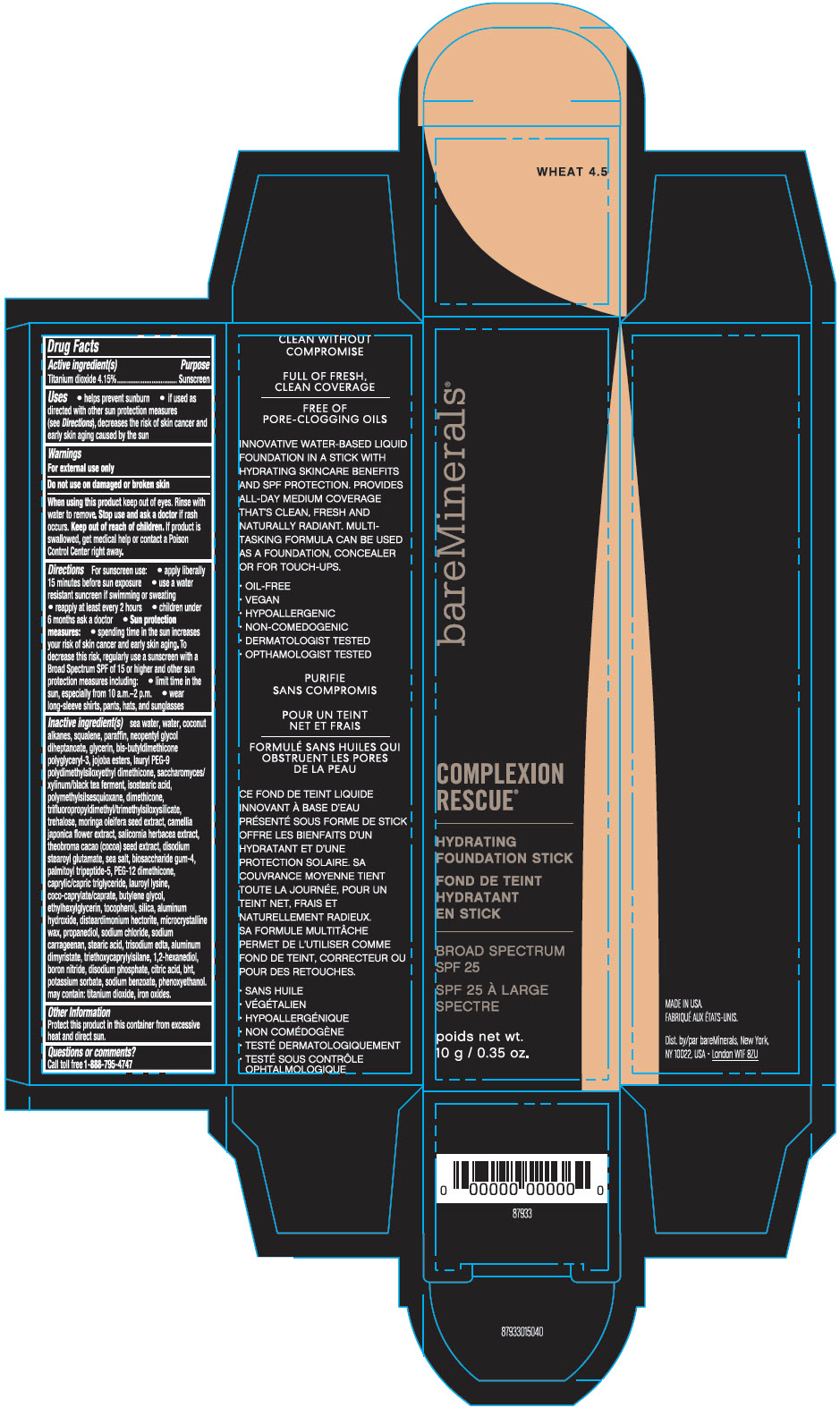 DRUG LABEL: bareMinerals Complexion Rescue Hydrating Foundation Broad Spectrum SPF 25 
NDC: 98132-254 | Form: STICK
Manufacturer: Bare Escentuals Beauty, Inc.
Category: otc | Type: HUMAN OTC DRUG LABEL
Date: 20191018

ACTIVE INGREDIENTS: Titanium Dioxide 415 mg/10 g
INACTIVE INGREDIENTS: SODIUM CHLORIDE; Water; Coconut Alkanes; Squalane; paraffin; neopentyl glycol diheptanoate; glycerin; HYDROGENATED JOJOBA OIL, RANDOMIZED; lauryl peg-9 polydimethylsiloxyethyl dimethicone; isostearic acid; POLYMETHYLSILSESQUIOXANE (4.5 MICRONS); dimethicone; trehalose; MORINGA OLEIFERA SEED OIL; CAMELLIA JAPONICA FLOWER; SALICORNIA EUROPAEA; COCOA; disodium stearoyl glutamate; Sea salt; biosaccharide gum-4; palmitoyl tripeptide-5; PEG-12 DIMETHICONE (300 CST); MEDIUM-CHAIN TRIGLYCERIDES; lauroyl lysine; coco-caprylate/caprate; butylene glycol; ethylhexylglycerin; tocopherol; SILICON DIOXIDE; ALUMINUM HYDROXIDE; disteardimonium hectorite; microcrystalline wax; propanediol; CARRAGEENAN SODIUM; stearic acid; EDETATE TRISODIUM; aluminum dimyristate; triethoxycaprylylsilane; 1,2-hexanediol; boron nitride; SODIUM PHOSPHATE, DIBASIC, ANHYDROUS; CITRIC ACID MONOHYDRATE; BUTYLATED HYDROXYTOLUENE; potassium sorbate; sodium benzoate; phenoxyethanol; FERRIC OXIDE RED

bareMinerals® Complexion Rescue® Hydrating Foundation Stick Broad Spectrum SPF 25

Drug Facts

Active ingredients

Titanium Dioxide 4.15%

Purpose

Sunscreen

Uses

- helps prevent sunburn
- if used as directed with other sun protection measures (see Directions), decreases the risk of skin cancer and early skin aging caused by the sun

Warnings

For external use only

Do not use on damaged or broken skin

When using this product keep out of eyes. Rinse with water to remove.

Stop use and ask a doctor if rash occurs.

Keep out of reach of children. If product is swallowed, get medical help or contact a Poison Control Center right away.

Directions

For sunscreen use:

- apply liberally 15 minutes before sun exposure
- use a water resistant sunscreen if swimming or sweating
- reapply at least every 2 hours
- children under 6 months: ask a doctor
- Sun Protection Measures. Spending time in the sun increases your risk of skin cancer and early skin aging. To decrease this risk, regularly use a sunscreen with a broad spectrum SPF of 15 or higher and other sun protection measures including:
  - limit time in the sun, especially from 10 a.m. – 2 p.m.
  - wear long-sleeve shirts, pants, hats, and sunglasses

Inactive Ingredients

sea water, water, coconut alkanes, squalane, paraffin, neopentyl glycol diheptanoate, glycerin, bis-butyldimethicone polyglyceryl-3, jojoba esters, lauryl peg-9 polydimethylsiloxyethyl dimethicone, saccharomyces/xylinum/black tea ferment, isostearic acid, polymethylsilsesquioxane, dimethicone, trifluoropropyldimethyl/trimethylsiloxysilicate, trehalose, moringa oleifera seed extract, camellia japonica flower extract, salicornia herbacea extract, theobroma cacao (cocoa) seed extract, disodium stearoyl glutamate, sea salt, biosaccharide gum-4, palmitoyl tripeptide-5, peg-12 dimethicone, caprylic/capric triglyceride, lauroyl lysine, coco-caprylate/caprate, butylene glycol, ethylhexylglycerin, tocopherol, silica, aluminum hydroxide, disteardimonium hectorite, microcrystalline wax, propanediol, sodium chloride, sodium carrageenan, stearic acid, trisodium edta, aluminum dimyristate, triethoxycaprylylsilane, 1,2-hexanediol, boron nitride, disodium phosphate, citric acid, bht, potassium sorbate, sodium benzoate, phenoxyethanol. may contain: titanium dioxide, iron oxides.

Other information

Protect this product in this container from excessive heat and direct sun.

Questions or comments?

Call toll free 1-800-795-4747

Dist. by bareMinerals, New York,
NY 10022, USA

PRINCIPAL DISPLAY PANEL - 10 g Tube Carton - Bamboo

bareMinerals®

COMPLEXION
RESCUE®

HYDRATING
FOUNDATION STICK

BROAD SPECTRUM
SPF 25

poids net wt.
10 g / 0.35 oz.

PRINCIPAL DISPLAY PANEL - 10 g Tube Carton - Birch

bareMinerals®

COMPLEXION
RESCUE®

HYDRATING
FOUNDATION STICK

BROAD SPECTRUM
SPF 25

poids net wt.
10 g / 0.35 oz.

PRINCIPAL DISPLAY PANEL - 10 g Tube Carton - Buttercream

bareMinerals®

COMPLEXION
RESCUE®

HYDRATING
FOUNDATION STICK

BROAD SPECTRUM
SPF 25

poids net wt.
10 g / 0.35 oz.

PRINCIPAL DISPLAY PANEL - 10 g Tube Carton - Cashew

bareMinerals®

COMPLEXION
RESCUE®

HYDRATING
FOUNDATION STICK

BROAD SPECTRUM
SPF 25

poids net wt.
10 g / 0.35 oz.

PRINCIPAL DISPLAY PANEL - 10 g Tube Carton - Cedar

bareMinerals®

COMPLEXION
RESCUE®

HYDRATING
FOUNDATION STICK

BROAD SPECTRUM
SPF 25

poids net wt.
10 g / 0.35 oz.

PRINCIPAL DISPLAY PANEL - 10 g Tube Carton - Chestnut

bareMinerals®

COMPLEXION
RESCUE®

HYDRATING
FOUNDATION STICK

BROAD SPECTRUM
SPF 25

poids net wt.
10 g / 0.35 oz.

PRINCIPAL DISPLAY PANEL - 10 g Tube Carton - Cinnamon

bareMinerals®

COMPLEXION
RESCUE®

HYDRATING
FOUNDATION STICK

BROAD SPECTRUM
SPF 25

poids net wt.
10 g / 0.35 oz.

PRINCIPAL DISPLAY PANEL - 10 g Tube Carton - Desert

bareMinerals®

COMPLEXION
RESCUE®

HYDRATING
FOUNDATION STICK

BROAD SPECTRUM
SPF 25

poids net wt.
10 g / 0.35 oz.

PRINCIPAL DISPLAY PANEL - 10 g Tube Carton - Dune

bareMinerals®

COMPLEXION
RESCUE®

HYDRATING
FOUNDATION STICK

BROAD SPECTRUM
SPF 25

poids net wt.
10 g / 0.35 oz.

PRINCIPAL DISPLAY PANEL - 10 g Tube Carton - Ginger

bareMinerals®

COMPLEXION
RESCUE®

HYDRATING
FOUNDATION STICK

BROAD SPECTRUM
SPF 25

poids net wt.
10 g / 0.35 oz.

PRINCIPAL DISPLAY PANEL - 10 g Tube Carton - Mahogany

bareMinerals®

COMPLEXION
RESCUE®

HYDRATING
FOUNDATION STICK

BROAD SPECTRUM
SPF 25

poids net wt.
10 g / 0.35 oz.

PRINCIPAL DISPLAY PANEL - 10 g Tube Carton - Natural

bareMinerals®

COMPLEXION
RESCUE®

HYDRATING
FOUNDATION STICK

BROAD SPECTRUM
SPF 25

poids net wt.
10 g / 0.35 oz.

PRINCIPAL DISPLAY PANEL - 10 g Tube Carton - Opal

bareMinerals®

COMPLEXION
RESCUE®

HYDRATING
FOUNDATION STICK

BROAD SPECTRUM
SPF 25

poids net wt.
10 g / 0.35 oz.

PRINCIPAL DISPLAY PANEL - 10 g Tube Carton - Sienna

bareMinerals®

COMPLEXION
RESCUE®

HYDRATING
FOUNDATION STICK

BROAD SPECTRUM
SPF 25

poids net wt.
10 g / 0.35 oz.

PRINCIPAL DISPLAY PANEL - 10 g Tube Carton - Spice

bareMinerals®

COMPLEXION
RESCUE®

HYDRATING
FOUNDATION STICK

BROAD SPECTRUM
SPF 25

poids net wt.
10 g / 0.35 oz.

PRINCIPAL DISPLAY PANEL - 10 g Tube Carton - Suede

bareMinerals®

COMPLEXION
RESCUE®

HYDRATING
FOUNDATION STICK

BROAD SPECTRUM
SPF 25

poids net wt.
10 g / 0.35 oz.

PRINCIPAL DISPLAY PANEL - 10 g Tube Carton - Tan

bareMinerals®

COMPLEXION
RESCUE®

HYDRATING
FOUNDATION STICK

BROAD SPECTRUM
SPF 25

poids net wt.
10 g / 0.35 oz.

PRINCIPAL DISPLAY PANEL - 10 g Tube Carton - Terra

bareMinerals®

COMPLEXION
RESCUE®

HYDRATING
FOUNDATION STICK

BROAD SPECTRUM
SPF 25

poids net wt.
10 g / 0.35 oz.

PRINCIPAL DISPLAY PANEL - 10 g Tube Carton - Vanilla

bareMinerals®

COMPLEXION
RESCUE®

HYDRATING
FOUNDATION STICK

BROAD SPECTRUM
SPF 25

poids net wt.
10 g / 0.35 oz.

PRINCIPAL DISPLAY PANEL - 10 g Tube Carton - Wheat

bareMinerals®

COMPLEXION
RESCUE®

HYDRATING
FOUNDATION STICK

BROAD SPECTRUM
SPF 25

poids net wt.
10 g / 0.35 oz.